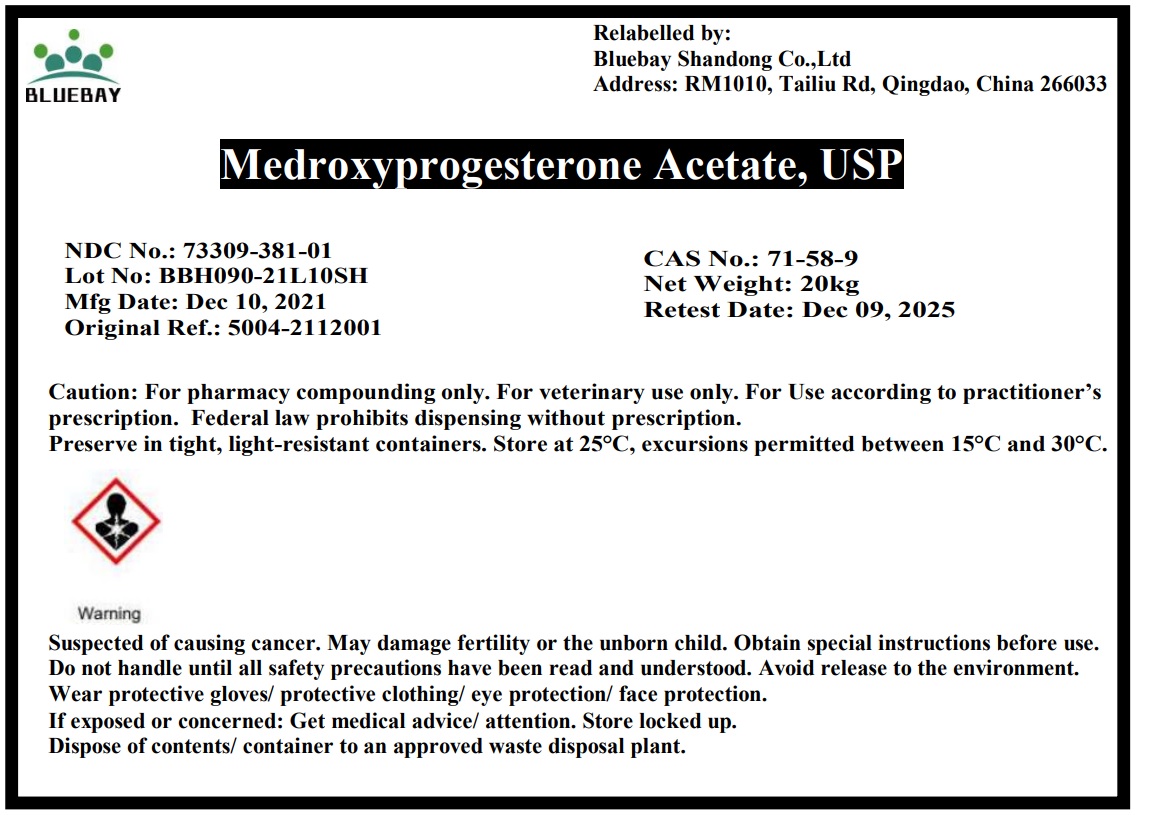 DRUG LABEL: Medroxyprogesterone acetate
NDC: 73309-381 | Form: POWDER
Manufacturer: BLUEBAY SHANDONG CO.,LTD
Category: other | Type: BULK INGREDIENT - ANIMAL DRUG
Date: 20220317

ACTIVE INGREDIENTS: MEDROXYPROGESTERONE ACETATE 1 kg/1 kg

Medroxyprogesterone
acetate